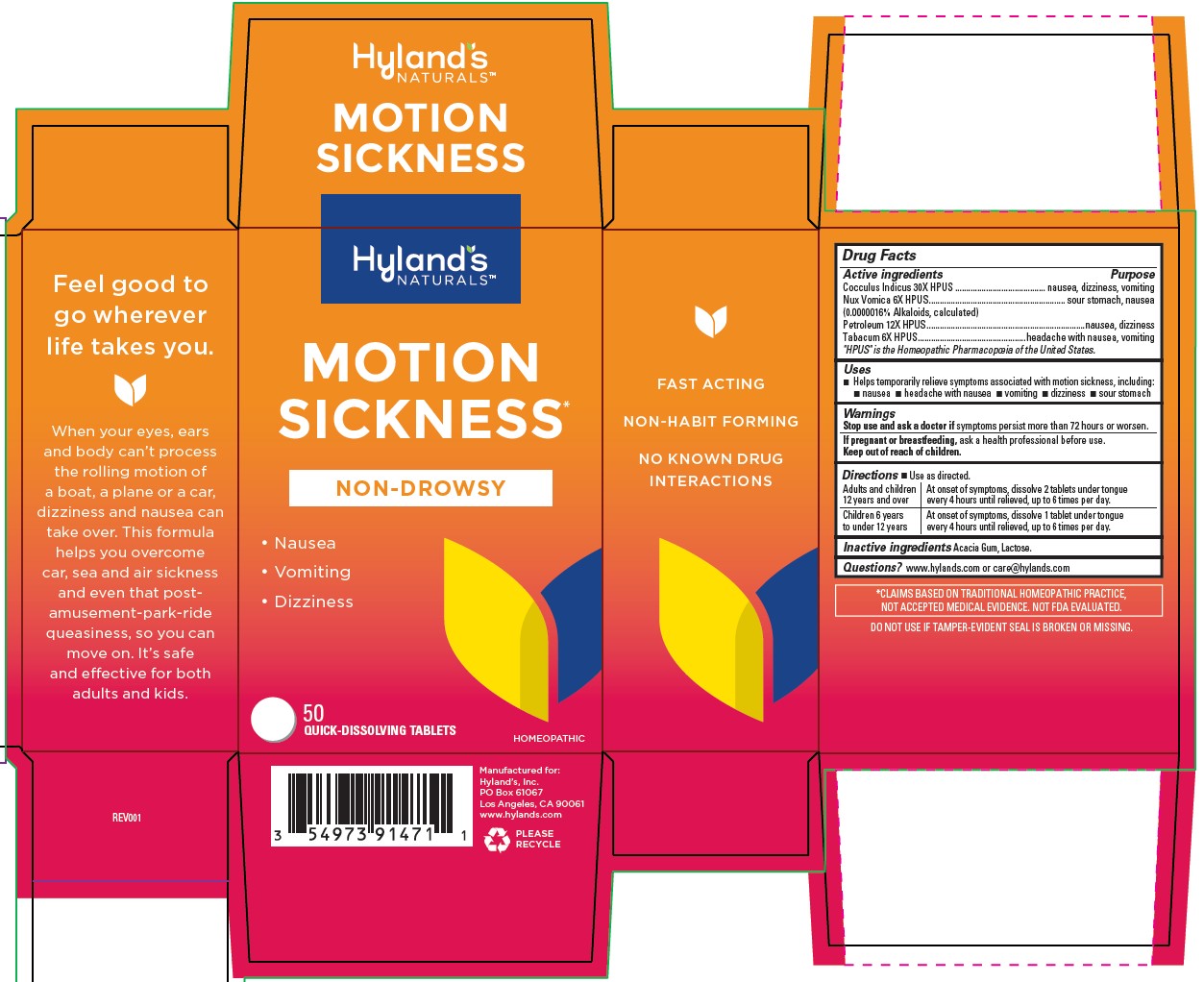 DRUG LABEL: Motion Sickness
NDC: 54973-9147 | Form: TABLET, SOLUBLE
Manufacturer: Hyland's Consumer Health Inc.
Category: homeopathic | Type: HUMAN OTC DRUG LABEL
Date: 20220908

ACTIVE INGREDIENTS: STRYCHNOS NUX-VOMICA SEED 6 [hp_X]/1 1; TOBACCO LEAF 6 [hp_X]/1 1; KEROSENE 12 [hp_X]/1 1; ANAMIRTA COCCULUS SEED 30 [hp_X]/1 1
INACTIVE INGREDIENTS: LACTOSE

Motion Sickness

PURPOSE

Temporarily relieves symptoms associated with motion sickness, including nausea, headache with nausea, vomiting, dizziness, sour stomach

Drug Facts

Active Ingredients | Purpose
Cocculus Indicus 30X HPUS | nausea, dizziness, vomiting
Nux Vomica 6X HPUS; (0.0000016% Alkaloids, calculated) | sour stomach, nausea
Petroleum 12X HPUS | nausea, dizziness
Tabacum 6X HPUS | headache with nausea, vomiting

"HPUS" is the Homeopathic Pharmacopoeia of the United States.

Uses

■ Temporarily relieves symptoms associated with motion sickness, including: ■ nausea ■ headache with nausea ■ vomiting ■ dizziness ■ sour stomach

Warnings

Stop use and ask a doctor if

symptoms persist more than 72 hours or worsen.

If pregnant or breastfeeding

Ask a health professional before use.

Directions

■ Use as directed.

Adults and children 12 years and over | At onset of symptoms, dissolve 2 tablets under tongue every 4 hours until relieved, up to 6 times per day.
Children 6 years to under 12 years | At onset of symptoms, dissolve 1 tablet under tongue every 4 hours until relieved, up to 6 times per day.

Inactive Ingredient

Acacia Gum, Lactose.

Questions?

www.hylands.com or care@hylands.com

Indications and Usage

 Temporarily relieves symptoms associated with motion sickness, including:
 nausea  headache with nausea  vomiting  dizziness  sour stomach

Dosage and Administration

Directions ■ Use as directed.

Adults and children 12 years and over | At onset of symptoms, dissolve 2 tablets under tongue every 4 hours until relieved, up to 6 times per day.
Children 6 years to under 12 years | At onset of symptoms, dissolve 1 tablet under tongue every 4 hours until relieved, up to 6 times per day.

Principal Display Panel

Hyland's

NATURALS™

MOTION

SICKNESS*

NON-DROWSY

• NAUSEA

• VOMITING

• DIZZINESS

50

QUICK-DISSOLVING TABLETS

HOMEOPATHIC